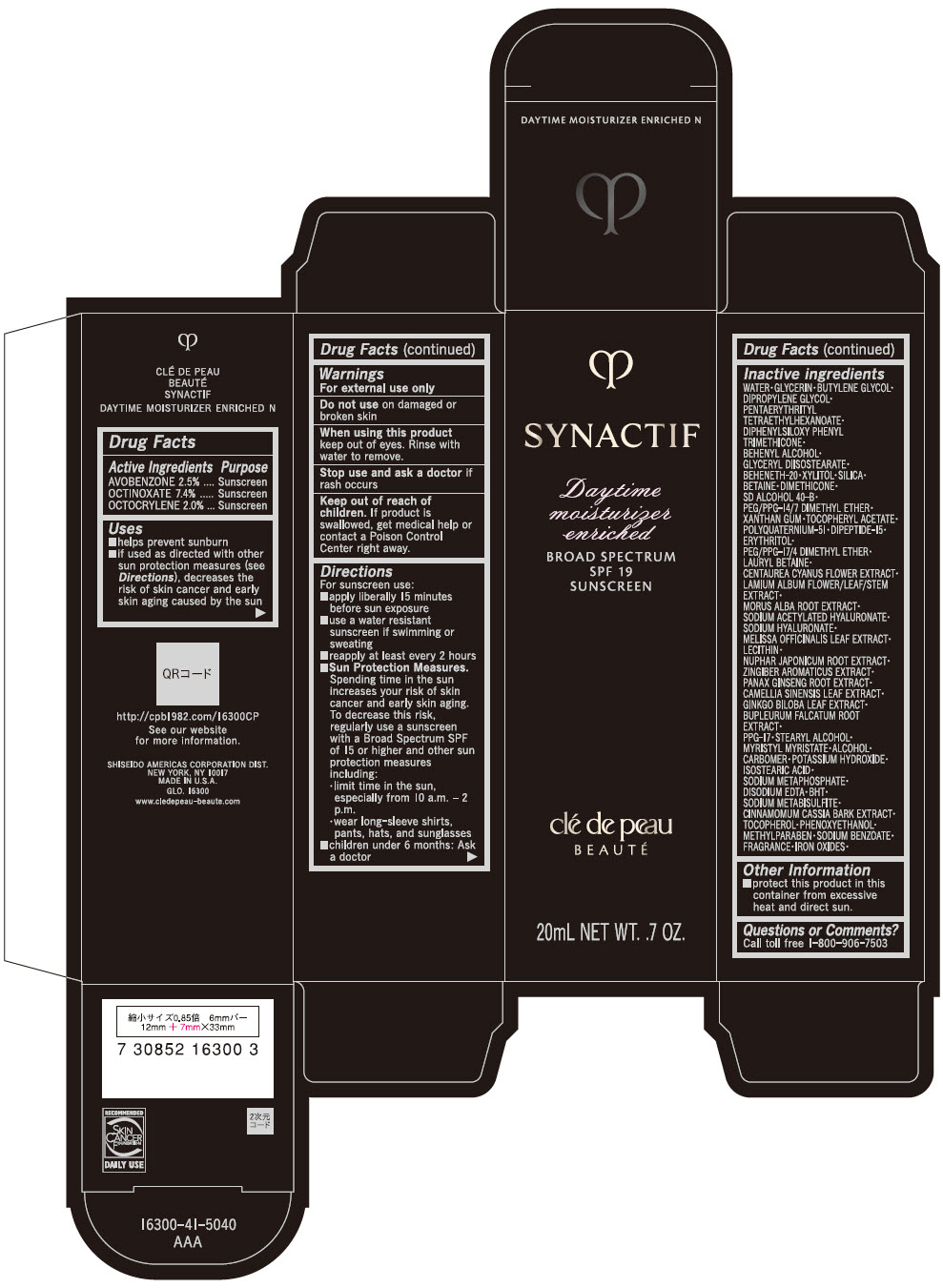 DRUG LABEL: cle de peau BEAUTE SYNACTIF DAYTIME MOISTURIZER ENRICHED n
NDC: 58411-889 | Form: EMULSION
Manufacturer: SHISEIDO AMERICAS CORPORATION
Category: otc | Type: HUMAN OTC DRUG LABEL
Date: 20260217

ACTIVE INGREDIENTS: AVOBENZONE 5 mg/200 mL; OCTINOXATE 14.8 mg/200 mL; OCTOCRYLENE 4 mg/200 mL
INACTIVE INGREDIENTS: WATER; GLYCERIN; BUTYLENE GLYCOL; DIPROPYLENE GLYCOL; PENTAERYTHRITYL TETRAETHYLHEXANOATE; DIPHENYLSILOXY PHENYL TRIMETHICONE; DOCOSANOL; GLYCERYL DIISOSTEARATE; BEHENETH-20; XYLITOL; SILICON DIOXIDE; BETAINE; DIMETHICONE; ALCOHOL; PEG/PPG-14/7 DIMETHYL ETHER; XANTHAN GUM; .ALPHA.-TOCOPHEROL ACETATE; POLYQUATERNIUM-51 (2-METHACRYLOYLOXYETHYL PHOSPHORYLCHOLINE/N-BUTYL METHACRYLATE; 3:7); DIGLYCINE; ERYTHRITOL; PEG/PPG-17/4 DIMETHYL ETHER; LAURYL BETAINE; CENTAUREA CYANUS FLOWER; LAMIUM ALBUM FLOWER; MORUS ALBA ROOT; SODIUM ACETYLATED HYALURONATE; HYALURONATE SODIUM; MELISSA OFFICINALIS LEAF; LECITHIN, SOYBEAN; NUPHAR JAPONICA ROOT; GINGER; ASIAN GINSENG; GREEN TEA LEAF; GINKGO; BUPLEURUM FALCATUM ROOT; PPG-17; STEARYL ALCOHOL; MYRISTYL MYRISTATE; CARBOMER HOMOPOLYMER TYPE C (ALLYL PENTAERYTHRITOL CROSSLINKED); POTASSIUM HYDROXIDE; ISOSTEARIC ACID; SODIUM METAPHOSPHATE; DISODIUM EDTA-COPPER; EDETATE DISODIUM; BUTYLATED HYDROXYTOLUENE; SODIUM METABISULFITE; CHINESE CINNAMON; .ALPHA.-TOCOPHEROL; PHENOXYETHANOL; METHYLPARABEN; SODIUM BENZOATE; FRAGRANCE 13576; FERRIC OXIDE RED; FERRIC OXIDE YELLOW

clé de peau BEAUTÉ SYNACTIF DAYTIME MOISTURIZER ENRICHED n

Drug Facts

ACTIVE INGREDIENT

Active ingredients | Purpose
AVOBENZONE 2.5% | Sunscreen
OCTINOXATE 7.4% | Sunscreen
OCTOCRYLENE 2.0% | Sunscreen

Uses

- helps prevent sunburn
- If used as directed with other sun protection measures (see Directions), decreases the risk of skin cancer and early skin aging caused by the sun

Warnings

For external use only

Do not useon damaged or broken skin

WHEN USING

When using this productkeep out of eyes. Rinse with water to remove.

Stop use and ask a doctorif rash occurs

Keep out of reach of children.If product is swallowed, get medical help or contact a Poison Control Center right away.

Directions

For sunscreen use:

- apply liberally 15 minutes before sun exposure
- use a water resistant sunscreen if swimming or sweating
- reapply at least every 2 hours
- Sun Protection Measures. Spending time in the sun increases your risk of skin cancer and early skin aging. To decrease this risk, regularly use a sunscreen with a Broad Spectrum SPF of 15 or higher and other sun protection measures including:
  - limit time in the sun, especially from 10 a.m. – 2 p.m.
  - wear long-sleeve shirts, pants, hats, and sunglasses
- children under 6 months: Ask a doctor

Inactive Ingredients

WATER•GLYCERIN•BUTYLENE GLYCOL•DIPROPYLENE GLYCOL•PENTAERYTHRITYL TETRAETHYLHEXANOATE•DIPHENYLSILOXY PHENYL TRIMETHICONE•BEHENYL ALCOHOL•GLYCERYL DIISOSTEARATE•BEHENETH-20•XYLITOL•SILICA•BETAINE•DIMETHICONE•SD ALCOHOL 40-B•PEG/PPG-14/7 DIMETHYL ETHER•XANTHAN GUM•TOCOPHERYL ACETATE•POLYQUATERNIUM-51•DIPEPTIDE-15•ERYTHRITOL•PEG/PPG-17/4 DIMETHYL ETHER•LAURYL BETAINE•CENTAUREA CYANUS FLOWER EXTRACT•LAMIUM ALBUM FLOWER/LEAF/STEM EXTRACT•MORUS ALBA ROOD EXTRACT•SODIUM ACETYLATED HYALURONATE•SODIUM HYALURONATE•MELISSA OFFICINALIS LEAF EXTRACT•LECITHIN•NUPHAR JAPONICUM ROOT EXTRACT•ZINGIBER AROMATICUS EXTRACT•PANAX GINSENG ROOT EXTRACT•CAMELLIA SINENSIS LEAF EXTRACT•GINKGO BILOBA LEAF EXTRACT•BUPLEURUM FALCATUM ROOT EXTRACT•PPG-17•STEARYL ALCOHOL•MYRISTYL MYRISTATE•ALCOHOL•CARBOMER•POTASSIUM HYDROXIDE•ISOSTEARIC ACID•SODIUM METAPHOSPHATE•DISODIUM EDTA•BHT•SODIUM METABISULFITE•CINNAMOMUM CASSIA BARK EXTRACT•TOCOPHEROL•PHENOXYETHANOL•METHYLPARABEN•SODIUM BENZOATE•FRAGRANCE•IRON OXIDES•

Other information

- protect this product in this container from excessive heat and direct sun.

Questions or Comments?

Call toll free 1-800-906-7503

PRINCIPAL DISPLAY PANEL - 20 mL Bottle Carton

SYNACTIF

Daytime
moisturizer
enriched

BROAD SPECTRUM
SPF 19
SUNSCREEN

clé de peau
BEAUTÉ

20mL NET WT. .7 OZ.